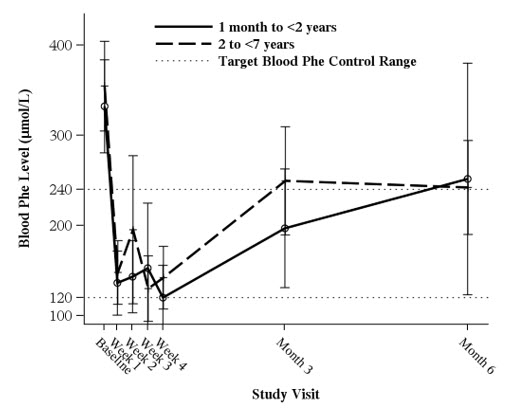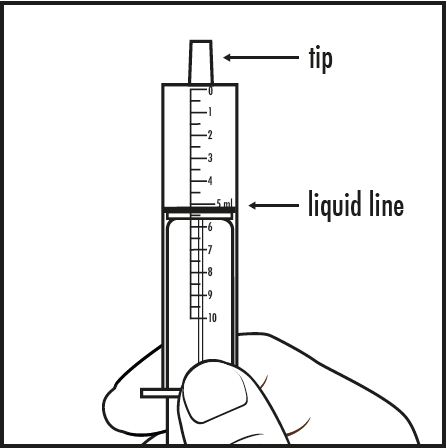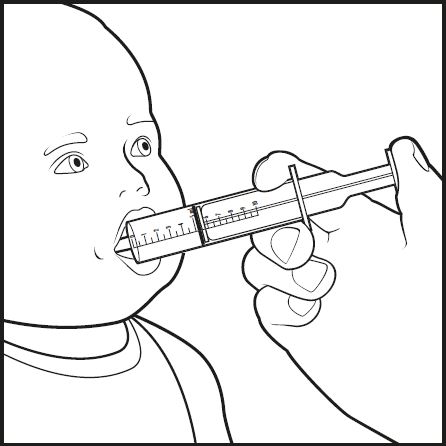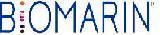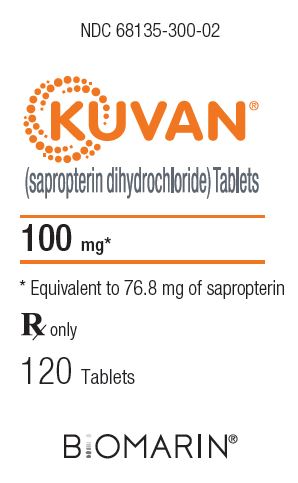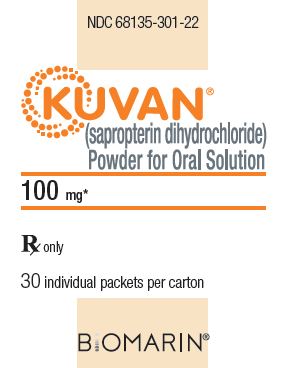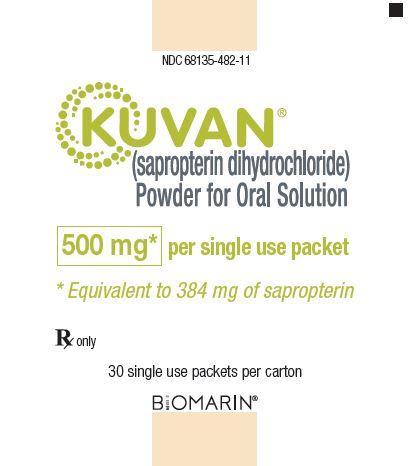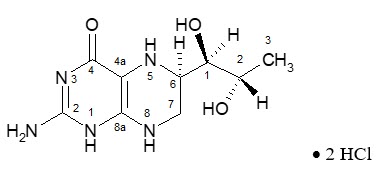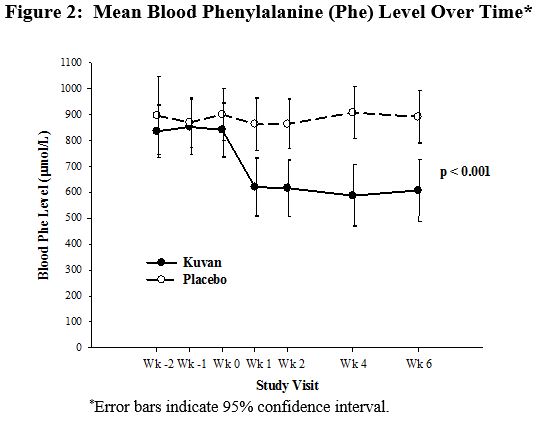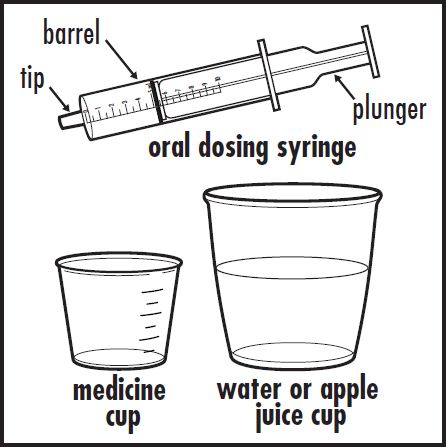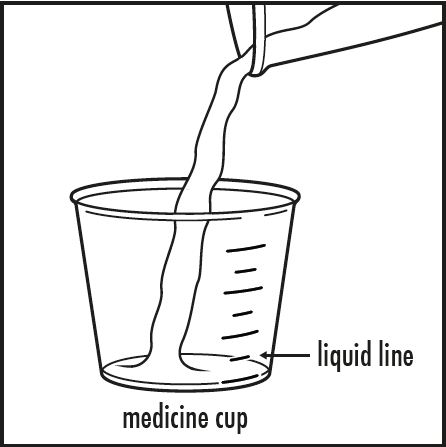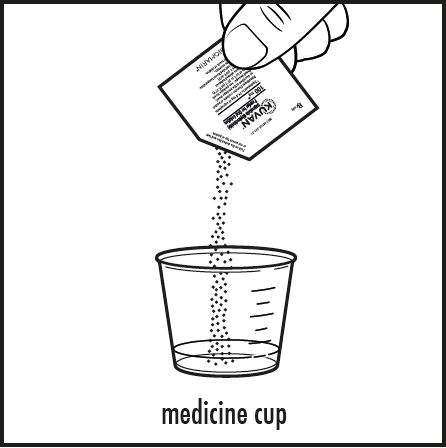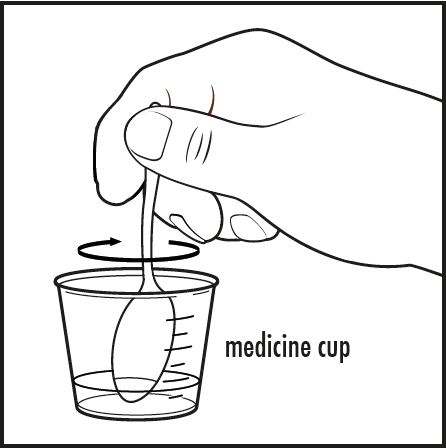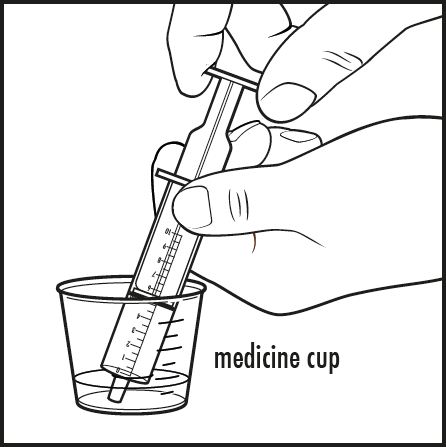 DRUG LABEL: Kuvan
NDC: 68135-300 | Form: TABLET
Manufacturer: BioMarin Pharmaceutical Inc.
Category: prescription | Type: HUMAN PRESCRIPTION DRUG LABEL
Date: 20240826

ACTIVE INGREDIENTS: SAPROPTERIN DIHYDROCHLORIDE 100 mg/1 1

HIGHLIGHTS OF PRESCRIBING INFORMATION

These highlights do not include all the information needed to use KUVAN safely and effectively.
See full prescribing information for KUVAN.
KUVAN (sapropterin dihydrochloride) tablets, for oral use
KUVAN (sapropterin dihydrochloride) powder, for oral solution
Initial U.S. Approval: 2007

1 INDICATIONS AND USAGE

KUVAN is a phenylalanine hydroxylase activator indicated to reduce blood phenylalanine (Phe) levels in adult and pediatric patients one month of age and older with hyperphenylalaninemia (HPA) due to tetrahydrobiopterin‑ (BH4‑) responsive Phenylketonuria (PKU). KUVAN is to be used in conjunction with a Phe‑restricted diet. (1)

2 DOSAGE AND ADMINISTRATION

All patients with PKU who are being treated with KUVAN should also be treated with a Phe-restricted diet, including dietary protein and Phe restriction. (2.1)

Starting Dosage

- Pediatric patients 1 month to 6 years: The recommended starting dosage of KUVAN is 10 mg/kg administered orally once daily. (2.2)
- Patients 7 years and older: The recommended starting dosage of KUVAN is 10 to 20 mg/kg administered orally once daily. (2.2)

Dosage Adjustment

- Doses of KUVAN may be adjusted in the range of 5 to 20 mg/kg taken once daily. (2.2)
- Monitor blood Phe regularly, especially in pediatric patients. (2.2, 5.3)

Preparation and Administration

- See the full prescribing information for preparation and administration instructions. (2.3)

3 DOSAGE FORMS AND STRENGTHS

- Tablets: 100 mg sapropterin dihydrochloride. (3)
- Powder for Oral Solution: 100 mg and 500 mg sapropterin dihydrochloride. (3)

4 CONTRAINDICATIONS

None. (4)

5 WARNINGS AND PRECAUTIONS

- Hypersensitivity Reactions Including Anaphylaxis: KUVAN is not recommended in patients with a history of anaphylaxis to KUVAN; discontinue treatment in patients who experience anaphylaxis and initiate appropriate medical treatment. Continue dietary Phe restrictions. (5.1)
- Upper Gastrointestinal Mucosal Inflammation: Monitor patients for signs and symptoms of these conditions including esophagitis and gastritis. (5.2)
- Hypophenylalaninemia: Pediatric patients younger than 7 years treated with KUVAN doses of 20 mg/kg per day are at increased risk for low levels of blood Phe compared with patients 7 years and older. (5.3)
- Monitoring Blood Phe Levels During Treatment: Ensure adequate blood Phe control and nutritional balance during treatment with KUVAN. Frequent blood monitoring is recommended, especially in pediatric patients. (5.4, 2.1)

- Lack of Biochemical Response to KUVAN Treatment: Response to KUVAN treatment cannot be pre-determined by laboratory (e.g., molecular) testing and can only be determined by a therapeutic trial of KUVAN. (5.5, 2.1)

- Interaction with Levodopa: Seizures, over-stimulation or irritability may occur; monitor patients for a change in neurologic status. (5.6, 7)
- Hyperactivity: Monitor patients for hyperactivity. (5.7)

6 ADVERSE REACTIONS

Most common adverse reactions (≥4%) are: headache, rhinorrhea, pharyngolaryngeal pain, diarrhea, vomiting, cough, and nasal congestion. (6.1)

To report SUSPECTED ADVERSE REACTIONS, contact BioMarin Pharmaceutical Inc. at 1-877-695-8826, or FDA at 1-800-FDA-1088 or www.fda.gov/medwatch.

7 DRUG INTERACTIONS

- Inhibitors of Folate Synthesis (e.g., methotrexate, valproic acid, phenobarbital, trimethoprim): Can decrease endogenous BH4 levels; monitor blood Phe levels more frequently and adjust KUVAN dosage as needed. (7)
- Drugs Affecting Nitric Oxide‑Mediated Vasorelaxation (e.g., PDE-5 inhibitors): Potential for vasorelaxation; monitor blood pressure. (7)

FULL PRESCRIBING INFORMATION

1 INDICATIONS AND USAGE

KUVAN® is indicated to reduce blood phenylalanine (Phe) levels in adult and pediatric patients one month of age and older with hyperphenylalaninemia (HPA) due to tetrahydrobiopterin- (BH4-) responsive Phenylketonuria (PKU). KUVAN is to be used in conjunction with a Phe-restricted diet.

2 DOSAGE AND ADMINISTRATION

2.1 Recommendations Prior to KUVAN Treatment

Treatment with KUVAN should be directed by physicians knowledgeable in the management of PKU.

All patients with PKU who are being treated with KUVAN should also be treated with a Phe-restricted diet, including dietary protein and Phe restriction.

2.2 Recommended Dosage and Administration

The recommended starting dosage of KUVAN is:

Pediatric Patients 1 month to 6 years: 10 mg/kg (actual body weight) administered orally once daily.

Patients 7 years and older: 10 to 20 mg/kg (actual body weight) administered orally once daily.

Administer KUVAN with a meal, preferably at the same time each day [see Clinical Pharmacology (12.3)].

A missed dose should be administered as soon as possible, but two doses should not be administered on the same day.

Evaluation Period

Existing dietary protein and Phe intake should not be modified during the evaluation period.

If a 10 mg/kg per day starting dose is used, then response to therapy is determined by change in blood Phe following treatment with KUVAN at 10 mg/kg per day for a period of up to 1 month. Blood Phe levels should be checked after 1 week of KUVAN treatment and periodically for up to a month. If blood Phe does not decrease from baseline at 10 mg/kg per day, the dose may be increased to 20 mg/kg per day. Patients whose blood Phe does not decrease after 1 month of treatment at 20 mg/kg per day do not show a biochemical response and treatment with KUVAN should be discontinued in these patients.

If a 20 mg/kg per day starting dose is used, then response to therapy is determined by change in blood Phe following treatment with KUVAN at 20 mg/kg per day for a period of 1 month. Blood Phe levels should be checked after 1 week of KUVAN treatment and periodically during the first month. Treatment should be discontinued in patients who do not show a biochemical response (blood Phe does not decrease) after 1 month of treatment at 20 mg/kg per day [see Warnings and Precautions (5.4)].

Dosage Adjustment

Once responsiveness to KUVAN has been established, the dosage may be adjusted within the range of 5 to 20 mg/kg per day according to biochemical response to therapy (blood Phe). Periodic blood Phe monitoring is recommended to assess blood Phe control, especially in pediatric patients [see Warnings and Precautions (5.3)].

2.3 Preparation and Administration Instructions

KUVAN Tablets

- KUVAN tablets may be swallowed either as whole tablets or dissolved in 120 to 240 mL of water or apple juice and taken orally within 15 minutes of dissolution.
- It may take a few minutes for the tablets to dissolve.
- To make the tablets dissolve faster, tablets may be stirred or crushed.
- The tablets may not dissolve completely. Patients may see small pieces floating on top of the water or apple juice. This is normal and safe for patients to swallow.
- If after drinking the medicine, patients still see pieces of the tablet in the container, more water or apple juice can be added to make sure all of the medicine is consumed.
- KUVAN tablets may also be crushed and then mixed in a small amount of soft foods such as apple sauce or pudding.

KUVAN Powder for Oral Solution

Patients weighing greater than 10 kg

- KUVAN powder for oral solution should be dissolved in 120 to 240 mL of water or apple juice and taken orally within 30 minutes of dissolution.
- KUVAN powder for oral solution may also be stirred in a small amount of soft food such as apple sauce or pudding.
- Empty the contents of the packet(s) in water, apple juice, or a small amount of soft foods and mix thoroughly. The powder should dissolve completely.

Patients weighing 10 kg or less (use 100 mg packets)

- For infants weighing 10 kg or less, KUVAN powder for oral solution can be dissolved in as little as 5 mL of water or apple juice and a portion of this solution corresponding to a 10 mg/kg dose may be administered orally via an oral dosing syringe.
- Table 1 provides dosing information for infants at the recommended starting dose of 10 mg/kg per day.
- Refer to Table 2 for dosing information at 20 mg/kg per day if dosage adjustment is needed.

Table 1: 10 mg/kg per day Dosing Table for Infants Weighing 10 kg or Less

Patient; Weight (kg) | Starting Dose: 10 mg/kg per day*
Patient; Weight (kg) | Dose (mg) | KUVAN Powder for Oral Solution; 100 mg Packets Dissolved† | Dilution Volume (mL)‡ | Administered Dose volume; (mL)§
1 | 10 | 1 | 10 | 1
2 | 20 | 1 | 10 | 2
3 | 30 | 1 | 10 | 3
4 | 40 | 1 | 10 | 4
5 | 50 | 1 | 10 | 5
6 | 60 | 1 | 5 | 3
7 | 70 | 1 | 5 | 3.5
8 | 80 | 1 | 5 | 4
9 | 90 | 1 | 5 | 4.5
10 | 100 | 1 | 5 | 5

*Starting dose for infants is 10 mg/kg per day. Dosing information for 20 mg/kg per day is provided in Table 2.

†Powder for oral solution provided in single use packets containing 100 mg KUVAN per packet.

‡Volume of water or apple juice to dissolve KUVAN Powder for Oral Solution.

§Discard remainder of mixture after volume to be administered is drawn.

Table 2: 20 mg/kg per day Dosing Table for Infants Weighing 10 kg or Less

Patient; Weight (kg) | 20 mg/kg per day
Patient; Weight (kg) | Dose (mg) | KUVAN Powder for Oral Solution; 100 mg Packets* Dissolved | Dilution Volume (mL)† | Administered Dose volume; (mL)§
1 | 20 | 1 | 5 | 1
2 | 40 | 1 | 5 | 2
3 | 60 | 1 | 5 | 3
4 | 80 | 1 | 5 | 4
5 | 100 | 1 | 5 | 5
6 | 120 | 2 | 5 | 3
7 | 140 | 2 | 5 | 3.5
8 | 160 | 2 | 5 | 4
9 | 180 | 2 | 5 | 4.5
10 | 200 | 2 | 5 | 5

*Powder for oral solution provided in single use packets containing 100 mg KUVAN per packet.

†Volume of water or apple juice to dissolve KUVAN Powder for Oral Solution.

§Discard remainder of mixture after volume to be administered is drawn.

3 DOSAGE FORMS AND STRENGTHS

KUVAN tablets are for oral use. Each tablet contains 100 mg of sapropterin dihydrochloride. Tablets are round, off-white to light yellow, mottled, and debossed with “177”.

KUVAN powder for oral solution is available as a unit dose packet containing 100 mg of sapropterin dihydrochloride and as a unit dose packet containing 500 mg of sapropterin dihydrochloride. The powder is off-white to yellow in color.

4 CONTRAINDICATIONS

None.

5 WARNINGS AND PRECAUTIONS

5.1 Hypersensitivity Reactions Including Anaphylaxis

KUVAN is not recommended in patients with a history of anaphylaxis to KUVAN. Hypersensitivity reactions, including anaphylaxis and rash, have occurred [see Adverse Reactions (6.2)]. Signs of anaphylaxis include wheezing, dyspnea, coughing, hypotension, flushing, nausea, and rash. Discontinue treatment with KUVAN in patients who experience anaphylaxis and initiate appropriate medical treatment. Continue dietary protein and Phe restriction in patients who experience anaphylaxis.

5.2 Upper Gastrointestinal Mucosal Inflammation

Gastrointestinal (GI) adverse reactions suggestive of upper GI mucosal inflammation have been reported with KUVAN. Serious adverse reactions included esophagitis and gastritis [see Adverse Reactions (6.2)]. If left untreated, these could lead to severe sequelae including esophageal stricture, esophageal ulcer, gastric ulcer, and bleeding and such complications have been reported in patients receiving KUVAN. Monitor patients for signs and symptoms of upper GI mucosal inflammation.

5.3 Hypophenylalaninemia

In clinical trials of KUVAN, some PKU patients experienced hypophenylalaninemia (low blood Phe) during treatment with KUVAN. In a clinical study of pediatric patients younger than 7 years old treated with KUVAN 20 mg/kg per day, the incidence of hypophenylalaninemia was higher than in clinical trials of older patients [see Adverse Reactions (6.1)].

5.4 Monitoring Blood Phe Levels During Treatment

Prolonged elevations of blood Phe levels in patients with PKU can result in severe neurologic damage, including severe intellectual disability, developmental delay, microcephaly, delayed speech, seizures, and behavioral abnormalities. Conversely, prolonged levels of blood Phe that are too low have been associated with catabolism and endogenous protein breakdown, which has been associated with adverse developmental outcomes. Active management of dietary Phe intake while taking KUVAN is required to ensure adequate Phe control and nutritional balance. Monitor blood Phe levels during treatment to ensure adequate blood Phe level control. Frequent blood monitoring is recommended in the pediatric population [see Dosage and Administration (2.2)].

5.5 Lack of Biochemical Response to KUVAN

Some patients with PKU do not show biochemical response (reduction in blood Phe) with treatment with KUVAN. In two clinical trials at a KUVAN dose of 20 mg/kg per day, 56% to 75% of pediatric PKU patients showed a biochemical response to KUVAN, and in one clinical trial at a dose of 10 mg/kg per day, 20% of adult and pediatric PKU patients showed a biochemical response to KUVAN [see Clinical Studies (14)].

Biochemical response to KUVAN treatment cannot generally be pre-determined by laboratory testing (e.g., molecular testing), and should be determined through a therapeutic trial (evaluation) of KUVAN response [see Dosage and Administration (2.2)].

5.6 Interaction with Levodopa

In a 10-year post-marketing safety surveillance program for a non-PKU indication using another sapropterin product, 3 patients with underlying neurological disorders experienced seizures, exacerbation of seizures, over-stimulation, and irritability during co-administration of levodopa and sapropterin. Monitor patients who are receiving levodopa for changes in neurological status during treatment with KUVAN [see Drug Interactions (7)].

5.7 Hyperactivity

In the KUVAN postmarketing safety surveillance program, 2 patients with PKU experienced hyperactivity when treated with KUVAN [see Adverse Reactions (6.2)]. Monitor patients for hyperactivity.

6 ADVERSE REACTIONS

6.1 Clinical Trials Experience

Because clinical trials are conducted under widely varying conditions, adverse reaction rates observed in the clinical trials of a drug cannot be directly compared to the rates in the clinical trials of another drug and may not reflect the rates observed in clinical practice.

PKU Clinical Studies

The safety of KUVAN was evaluated in 7 clinical studies in patients with PKU (aged 1 month to 50 years) [see Clinical Studies (14)].

In Studies 1-4 (controlled and uncontrolled studies), 579 patients with PKU aged 4 to 49 years received KUVAN in doses ranging from 5 to 20 mg/kg per day for lengths of treatment ranging from 1 to 164 weeks. The patient population was evenly distributed in gender, and approximately 95% of patients were Caucasian. The most common adverse reactions (≥4% of patients) were headache, rhinorrhea, pharyngolaryngeal pain, diarrhea, vomiting, cough, and nasal congestion.

The data described in Table 3 reflect exposure of 74 patients with PKU to KUVAN at doses of 10 to 20 mg/kg per day for 6 to 10 weeks in two double-blind, placebo-controlled clinical trials (Studies 2 and 4).

Table 3 enumerates adverse reactions occurring in at least 4% of patients treated with KUVAN in the double-blind, placebo-controlled clinical trials described above.

Table 3: Summary of Adverse Reactions Occurring in ≥4% of Patients in Placebo-Controlled Clinical Studies with KUVAN

MedDRA Preferred Term | Treatment
MedDRA Preferred Term | KUVAN; (N=74) | Placebo; (N=59)
 | No. Patients (%) | No. Patients (%)
Headache | 11 (15) | 8 (14)
Rhinorrhea | 8 (11) | 0
Pharyngolaryngeal pain | 7 (10) | 1 (2)
Diarrhea | 6 (8) | 3 (5)
Vomiting | 6 (8) | 4 (7)
Cough | 5 (7) | 3 (5)
Nasal congestion | 3 (4) | 0

In open-label, uncontrolled clinical trials (Studies 1 and 3) all patients received KUVAN in doses of 5 to 20 mg/kg per day, and adverse reactions were similar in type and frequency to those reported in the double-blind, placebo-controlled clinical trials [see Clinical Studies (14)].

In Study 5, 65 pediatric patients with PKU aged 1 month to 6 years received KUVAN 20 mg/kg per day for 6 months. Adverse reactions in these patients were similar in frequency and type as those seen in other KUVAN clinical trials except for an increased incidence of low Phe levels. Twenty-five percent (16 out of 65) of patients developed Phe levels below normal for age [see Warnings and Precautions (5.3), Use In Specific Populations (8.4), and Clinical Studies (14)].

In Study 6, a long term, open-label, extension study of 111 patients aged 4 to 50 years, receiving KUVAN in doses ranging from 5 to 20 mg/kg per day, adverse reactions were similar in type and frequency to those reported in the previous clinical studies. Fifty-five patients received KUVAN both as dissolved and intact tablets. There were no notable differences in the incidence or severity of adverse reactions between the two methods of administration. The mean (± SD) exposure to sapropterin for the entire study population was 659 ± 221 days (maximum 953 days).

In Study 7, 27 pediatric patients with PKU aged 0 to 4 years received KUVAN 10 mg/kg per day or 20 mg/kg per day. Adverse reactions were similar in type and frequency to those observed in other clinical trials, with the addition of rhinitis, which was reported in 2 subjects (7.4%).

Safety Experience from Clinical Studies for Non-PKU Indications

Approximately 800 healthy subjects and patients with disorders other than PKU, some of whom had underlying neurologic disorders or cardiovascular disease, have been administered a different formulation of the same active ingredient (sapropterin) in approximately 19 controlled and uncontrolled clinical trials. In these clinical trials, subjects were administered sapropterin at doses ranging from 1 to 100 mg/kg per day for lengths of exposure from 1 day to 2 years. Serious and severe adverse reactions (regardless of causality) during sapropterin administration were seizures, exacerbation of seizures [see Warnings and Precautions (5.3)], dizziness, gastrointestinal bleeding, post-procedural bleeding, headache, irritability, myocardial infarction, overstimulation, and respiratory failure. Common adverse reactions were headache, peripheral edema, arthralgia, polyuria, agitation, dizziness, nausea, pharyngitis, abdominal pain, upper abdominal pain, and upper respiratory tract infection.

6.2 Postmarketing Experience

The following adverse reactions have been reported during post-approval use of KUVAN. Because these reactions are reported voluntarily from a population of uncertain size, it is not always possible to reliably estimate their frequency or establish a causal relationship to drug exposure.

Hypersensitivity reactions including anaphylaxis and rash: Most hypersensitivity reactions occurred within several days of initiating treatment [see Warnings and Precautions (5.1)].

Gastrointestinal reactions: esophagitis, gastritis, oropharyngeal pain, pharyngitis, esophageal pain, abdominal pain, dyspepsia, nausea, and vomiting [see Warnings and Precautions (5.2)].

Hyperactivity: Two cases have been reported. In one case, the patient received an accidental overdosage of KUVAN [see Warnings and Precautions (5.6), Overdosage (10)].

7 DRUG INTERACTIONS

Table 4 includes drugs with clinically important drug interactions when administered with sapropterin dihydrochloride and instructions for preventing or managing them.

Table 4: Clinically Relevant Drug Interactions

Levodopa
Clinical Impact | Sapropterin dihydrochloride may increase the availability of tyrosine, a precursor of levodopa. Neurologic events were reported postmarketing in patients receiving sapropterin and levodopa concomitantly for a non-PKU indication [see Warnings and Precautions (5.5)].
Intervention | Monitor patients for a change in neurologic status.
Inhibitors of Folate Synthesis (e.g., methotrexate, valproic acid, phenobarbital, trimethoprim)
Clinical Impact | In vitro and in vivo nonclinical data suggest that drugs that inhibit folate synthesis may decrease the bioavailability of endogenous BH4 by inhibiting the enzyme dihydrofolate reductase, which is involved in the recycling (regeneration) of BH4. This reduction in net BH4 levels may increase Phe levels.
Intervention | Consider monitoring blood Phe levels more frequently during concomitant administration. An increased dosage of KUVAN may be necessary to achieve a biochemical response.
Drugs Affecting Nitric Oxide‑Mediated Vasorelaxation (e.g., PDE-5 inhibitors such as sildenafil, vardenafil, or tadalafil)
Clinical Impact | Both sapropterin dihydrochloride and PDE-5 inhibitors may induce vasorelaxation. A reduction in blood pressure could occur; however, the combined use of these medications has not been evaluated in humans.
Intervention | Monitor blood pressure.

8 USE IN SPECIFIC POPULATIONS

8.1 Pregnancy

Risk Summary

Available data from pregnancy safety studies, pharmacovigilance, and published case reports with KUVAN use during pregnancy have not identified a drug-associated risk of major birth defects, miscarriage, or adverse maternal or fetal outcomes (see Data). Uncontrolled blood phenylalanine concentrations before and during pregnancy are associated with an increased risk of adverse pregnancy outcomes and fetal adverse effects (see Clinical Considerations).

An embryo-fetal development study with sapropterin dihydrochloride in rats using oral doses up to 3 times the maximum recommended human dose (MRHD) given during the period of organogenesis showed no effects. In a rabbit study using oral administration of sapropterin dihydrochloride during the period of organogenesis, a rare defect, holoprosencephaly, was noted at 10 times the MRHD.

All pregnancies have a background risk of major birth defects, pregnancy loss, or other adverse pregnancy outcomes. In the U.S. general population, the estimated background risk of major birth defects and miscarriage in clinically recognized pregnancies is 2 to 4% and 15 to 20%, respectively. The estimated background risk of major birth defects and miscarriage in pregnant women with PKU who maintain blood phenylalanine concentrations greater than 600 micromol/L during pregnancy is greater than the corresponding background risk for pregnant women without PKU.

Clinical Considerations

Disease-Associated Maternal and/or Embryo‑Fetal Risk

Uncontrolled blood phenylalanine concentrations before and during pregnancy are associated with an increased risk of adverse pregnancy outcomes and fetal adverse effects. To reduce the risk of hyperphenylalaninemia-induced fetal adverse effects, blood phenylalanine concentrations should be maintained between 120 and 360 micromol/L during pregnancy and during the 3 months before conception [see Dosage and Administration 2.2)].

Data

Human Data

Uncontrolled Maternal PKU

Available data from the Maternal Phenylketonuria Collaborative Study on 468 pregnancies and 331 live births in PKU‑affected women demonstrated that uncontrolled Phe levels above 600 micromol/L are associated with a very high incidence of neurological, cardiac, facial dysmorphism, and growth anomalies. Control of blood phenylalanine during pregnancy is essential to reduce the incidence of Phe-induced teratogenic effects.

Pregnancy Registry Data

Available data from pregnancy sub-registries within the Phenylketonuria Developmental Outcomes and Safety (PKUDOS) Registry and the KUVAN Adult Maternal Pediatric European Registry (KAMPER) have identified 72 live births (79 pregnancies) in women with PKU exposed to sapropterin during pregnancy. Three birth defects were reported, including one case each of microcephaly, cleft palate, and tongue tie. The two major birth defects (microcephaly and cleft palate) were associated with Phe levels greater than 360 micromol/L during pregnancy.

Animal Data

No effects on embryo-fetal development were observed in a reproduction study in rats using oral doses of up to 400 mg/kg per day sapropterin dihydrochloride (about 3 times the MRHD of 20 mg/kg per day, based on body surface area) administered during the period of organogenesis. However, in a rabbit reproduction study, oral administration of a maximum dose of 600 mg/kg per day (about 10 times the MRHD, based on body surface area) during the period of organogenesis was associated with a non-statistically significant increase in the incidence of holoprosencephaly in two high dose-treated litters (4 fetuses), compared to one control-treated litter (1 fetus).

8.2 Lactation

Risk Summary

There are insufficient data to assess the presence of sapropterin in human milk and no data on the effects on milk production. In postmarketing pregnancy registries, 13 infants were exposed to KUVAN through breastfeeding. No lactation-related safety concerns were reported in infants of mothers nursing during maternal treatment with KUVAN. There are no data on the effects on milk production. Sapropterin is present in the milk of lactating rats following intravenous administration, but not following oral administration.

The developmental and health benefits of breastfeeding should be considered along with the mother's clinical need for KUVAN and any potential adverse effects on the breastfed child from KUVAN or from the underlying maternal condition.

8.4 Pediatric Use

Pediatric patients with PKU, ages 1 month to 16 years, have been treated with KUVAN in clinical trials [see Clinical Studies (14)].

The efficacy and safety of KUVAN have not been established in neonates. The safety of KUVAN has been established in children younger than 4 years in trials of 6 months duration and in children 4 years and older in trials of up to 3 years in length [see Adverse Reactions (6.1)].

In children aged 1 month and older, the efficacy of KUVAN has been demonstrated in trials of 6 weeks or less in duration [see Clinical Studies (14)].

In a multicenter, open-label, single arm study, 57 patients aged 1 month to 6 years who were defined as KUVAN responders after 4 weeks of KUVAN treatment and Phe dietary restriction were treated for 6 months with KUVAN at 20 mg/kg per day. The effectiveness of KUVAN alone on reduction of blood Phe levels beyond 4 weeks could not be determined due to concurrent changes in dietary Phe intake during the study. Mean (±SD) blood Phe values over time for patients aged 1 month to <2 years and 2 to <7 years are shown in Figure 1.

Figure 1: Mean Blood Phe Level Over Time by Age (years) (N=57)

*Error bars indicate 95% confidence interval.

8.5 Geriatric Use

Clinical studies of KUVAN in patients with PKU did not include patients aged 65 years and older. It is not known whether these patients respond differently than younger patients.

10 OVERDOSAGE

Two unintentional overdosages with KUVAN have been reported. One adult patient in a KUVAN clinical trial received a single KUVAN dose of 4,500 mg (36 mg/kg) instead of 2,600 mg (20 mg/kg). The patient reported mild headache and mild dizziness immediately after taking the dose; both symptoms resolved within 1 hour with no treatment intervention. There were no associated laboratory test abnormalities. The patient suspended therapy for 24 hours and then restarted KUVAN with no reports of abnormal signs or symptoms. In postmarketing, one pediatric patient received KUVAN doses of 45 mg/kg per day instead of 20 mg/kg per day. The patient reported hyperactivity that began at an unspecified time after overdosage and resolved after the KUVAN dose was reduced to 20 mg/kg per day.

In a clinical study to evaluate the effects of KUVAN on cardiac repolarization, a single supra-therapeutic dose of 100 mg/kg (5 times the maximum recommended dose) was administered to 54 healthy adults. No serious adverse reactions were reported during the study. The only adverse reactions reported in more than 1 subject who received the supra-therapeutic dose were upper abdominal pain (6%) and dizziness (4%). A dose-dependent shortening of the QT interval was observed [see Clinical Pharmacology (12.2)].

Patients should be advised to notify their physicians in cases of overdosage.

11 DESCRIPTION

KUVAN (sapropterin dihydrochloride) is an orally administered Phenylalanine Hydroxylase activator (or PAH activator). Sapropterin dihydrochloride, the active pharmaceutical ingredient in KUVAN, is a synthetic preparation of the dihydrochloride salt of naturally occurring tetrahydrobiopterin (BH4). Sapropterin dihydrochloride is an off-white to light yellow crystals or crystalline powder.

The chemical name of sapropterin dihydrochloride is (6R)-2-amino-6-[(1R,2S)-1,2-dihydroxypropyl]-5,6,7,8-tetrahydro-4(1H)-pteridinone dihydrochloride and the molecular formula is C9H15N5O3·2HCl with a molecular weight of 314.17.

Sapropterin dihydrochloride has the following structural formula:

KUVAN is supplied as tablets and powder for oral solution containing 100 mg of sapropterin dihydrochloride (equivalent to 76.8 mg of sapropterin base). KUVAN is also supplied as powder for oral solution containing 500 mg of sapropterin dihydrochloride (equivalent to 384 mg of sapropterin base).

Tablets are round, off-white to light yellow, mottled, and debossed with “177”. Each tablet contains the following inactive ingredients: ascorbic acid (USP), crospovidone (NF), dibasic calcium phosphate (USP), D-mannitol (USP), riboflavin (USP), and sodium stearyl fumarate (NF).

KUVAN powder for oral solution is off-white to yellow in color. Each unit dose packet contains the following inactive ingredients: ascorbic acid (USP), D-mannitol (USP), potassium citrate (USP), and sucralose (NF).

12 CLINICAL PHARMACOLOGY

12.1 Mechanism of Action

KUVAN is a synthetic form of BH4, the cofactor for the enzyme phenylalanine hydroxylase (PAH). PAH hydroxylates Phe through an oxidative reaction to form tyrosine. In patients with PKU, PAH activity is absent or deficient. Treatment with BH4 can activate residual PAH enzyme activity, improve the normal oxidative metabolism of Phe, and decrease Phe levels in some patients.

12.2 Pharmacodynamics

In PKU patients who are responsive to BH4 treatment, blood Phe levels decrease within 24 hours after a single administration of sapropterin dihydrochloride, although maximal effect on Phe level may take up to a month, depending on the patient. A single daily dose of KUVAN is adequate to maintain stable blood Phe levels over a 24-hour period. Twelve patients with blood Phe levels ranging from 516 to 986 μmol/L (mean 747 ± 153 μmol/L) were assessed with 24‑hour blood Phe level monitoring following a daily morning dose of 10 mg/kg per day. The blood Phe level remained stable during a 24‑hour observation period. No substantial increases in blood Phe levels were observed following food intake throughout the 24-hour period.

KUVAN dose-response relationship was studied in an open-label, forced titration study at doses of 5 mg/kg per day, then 20 mg/kg per day, and then 10 mg/kg per day (Study 3) [see Clinical Studies (14.1)]. Individual blood Phe levels were highly variable among patients. The mean blood Phe level observed at the end of each 2-week dosing period decreased as the dose of sapropterin dihydrochloride increased, demonstrating an inverse relationship between the dose of sapropterin dihydrochloride and mean blood Phe levels.

Cardiac Electrophysiology

A thorough QTc study was performed in 56 healthy adults. This randomized, placebo and active controlled crossover study was conducted to determine if a single supra-therapeutic (100 mg/kg) dose of KUVAN or a single therapeutic dose (20 mg/kg) of KUVAN had an effect on cardiac repolarization. In this study, KUVAN was administered after dissolving tablets in water under fed condition. This study demonstrated a dose-dependent shortening of the QT interval. The maximum placebo-subtracted mean change from baseline of the QTc interval was -3.69 and -8.32 ms (lower bound of 90% CI: -5.3 and -10.6 ms) at 20 and 100 mg/kg, respectively.

12.3 Pharmacokinetics

Studies in healthy subjects have shown comparable absorption of sapropterin when tablets are dissolved in water or orange juice and taken under fasted conditions. Administration of dissolved tablets after a high-fat/high-calorie meal resulted in mean increases in Cmax of 84% and AUC of 87% (dissolved in water). However, there was extensive variability in individual subject values for Cmax and AUC across the different modes of administration and meal conditions. In the clinical trials of KUVAN, drug was administered in the morning as a dissolved tablet without regard to meals. The mean elimination half-life in PKU patients was approximately 6.7 hours (range 3.9 to 17 hours), comparable with values seen in healthy subjects (range 3.0 to 5.3 hours).

A study in healthy adults with 10 mg/kg of KUVAN demonstrated that the absorption via intact tablet administration was 40% greater than via dissolved tablet administration under fasted conditions based on AUC0-t. The administration of intact tablets under fed conditions resulted in an approximately 43% increase in the extent of absorption compared to fasted conditions based on AUC0-t [see Dosage and Administration (2.3)].

Population pharmacokinetic analysis of sapropterin including patients from 1 month to 49 years of age showed that body weight is the only covariate substantially affecting clearance or distribution volume (see Table 5). Pharmacokinetics in patients >49 years of age have not been studied.

Table 5: Apparent Plasma Clearance by Age

Parameter | 0 to <1 yr*; (N=10) | 1 to <6 yr*; (N=57) | 6 to <12 yr†; (N=23) | 12 to <18 yr†; (N=24) | ≥18 yr†; (N=42)
CL/F (L/hr/kg); Mean ± SD; (Median) | 81.5 ± 92.4 (53.6) | 50.7 ± 20.1 (48.4) | 51.7 ± 21.9 (47.4) | 39.2 ± 9.3 (38.3) | 37.9 ± 20.2 (31.8)

*Evaluated at 20 mg/kg per day dose.

†Evaluated at 5, 10, or 20 mg/kg per day doses.

Metabolism

Sapropterin is a synthetic form of tetrahydrobiopterin (BH4) and is expected to be metabolized and recycled by the same endogenous enzymes. In vivo endogenous BH4 is converted to quinoid dihydrobiopterin and is metabolized to dihydrobiopterin and biopterin. The enzymes dihydrofolate reductase and dihydropteridine reductase are responsible for the metabolism and recycling of BH4.

Drug Interaction Studies

Clinical Studies

In healthy subjects, administration of a single dose of KUVAN at the maximum therapeutic dose of 20 mg/kg had no effect on the pharmacokinetics of a single dose of digoxin (P-gp substrate) administered concomitantly.

In Vitro Studies Where Drug Interaction Potential Was Not Further Evaluated Clinically

The potential for sapropterin to induce or inhibit cytochrome P450 enzymes was evaluated in in vitro studies which showed sapropterin did not inhibit CYP 1A2, 2B6, 2C8, 2C9, 2C19, 2D6, or 3A4/5, nor induce CYP 1A2, 2B6, or 3A4/5.

In vitro sapropterin did not inhibit OAT1, OAT3, OCT2, MATE1, and MATE2-K transporters. The potential for sapropterin to inhibit OATP1B1 and OATP1B3 has not been adequately studied. In vitro, sapropterin inhibits breast cancer resistance protein (BCRP) but the potential for a clinically significant increase in systemic exposure of BCRP substrates by KUVAN appears to be low.

13 NONCLINICAL TOXICOLOGY

13.1 Carcinogenesis, Mutagenesis, Impairment of Fertility

A 2-year carcinogenicity study was conducted in F-344 rats, and a 78-week carcinogenicity study was conducted in CD-1 mice. In the 104-week oral carcinogenicity study in rats, sapropterin dihydrochloride doses of 25, 80, and 250 mg/kg per day (0.2, 0.7, and 2 times the maximum recommended human dose of 20 mg/kg per day, respectively, based on body surface area) were used. In the 78-week oral carcinogenicity study in mice, sapropterin dihydrochloride doses of 25, 80, and 250 mg/kg per day (0.1, 0.3, and 2 times the recommended human dose, respectively, based on body surface area) were used. In the 2‑year rat carcinogenicity study, there was a statistically significant increase in the incidence of benign adrenal pheochromocytoma in male rats treated with the 250 mg/kg per day (about 2 times the maximum recommended human dose, based on body surface area) dose, as compared to vehicle treated rats. The mouse carcinogenicity study showed no evidence of a carcinogenic effect, but the study was not ideal due to its duration of 78 instead of 104 weeks.

Sapropterin dihydrochloride was genotoxic in the in vitro Ames test at concentrations of 625 µg (TA98) and 5000 µg (TA100) per plate, without metabolic activation. However, no genotoxicity was observed in the in vitro Ames test with metabolic activation. Sapropterin dihydrochloride was genotoxic in the in vitro chromosomal aberration assay in Chinese hamster lung cells at concentrations of 0.25 and 0.5 mM. Sapropterin dihydrochloride was not mutagenic in the in vivo micronucleus assay in mice at doses up to 2000 mg/kg per day (about 8 times the maximum recommended human dose of 20 mg/kg per day, based on body surface area). Sapropterin dihydrochloride, at oral doses up to 400 mg/kg per day (about 3 times the maximum recommended human dose, based on body surface area) was found to have no effect on fertility and reproductive function of male and female rats.

14 CLINICAL STUDIES

The efficacy of KUVAN was evaluated in five clinical studies in patients with PKU.

Study 1 was a multicenter, open-label, uncontrolled clinical trial of 489 patients with PKU, ages 8 to 48 years (mean 22 years), who had baseline blood Phe levels ≥ 450 μmol/L and who were not on Phe-restricted diets. All patients received treatment with KUVAN 10 mg/kg per day for 8 days. For the purposes of this study, response to KUVAN treatment was defined as a ≥ 30% decrease in blood Phe from baseline. At Day 8, 96 patients (20%) were identified as responders.

Study 2 was a multicenter, double-blind, placebo-controlled study of 88 patients with PKU who responded to KUVAN in Study 1. After a washout period from Study 1, patients were randomized equally to either KUVAN 10 mg/kg per day (N=41) or placebo (N=47) for 6 weeks. Efficacy was assessed by the mean change in blood Phe level from baseline to Week 6 in the KUVAN-treated group as compared to the mean change in the placebo group.

The results showed that at baseline, the mean (±SD) blood Phe level was 843 (±300) μmol/L in the KUVAN-treated group and 888 (±323) μmol/L in the placebo group. At Week 6, the KUVAN treated group had a mean (±SD) blood Phe level of 607 (±377) μmol/L, and the placebo group had a mean blood Phe level of 891 (±348) μmol/L. At Week 6, the KUVAN- and placebo treated groups had mean changes in blood Phe level of –239 and 6 μmol/L, respectively (mean percent changes of –29% (±32) and 3% (±33), respectively). The difference between the groups was statistically significant (p < 0.001) (Table 6).

Table 6: Blood Phe Results in Study 2

 | Sapropterin (N=41) | Placebo (N=47)
Baseline Blood Phe Level* (μmol/L)
Mean (±SD) | 843 (±300) | 888 (±323)
Percentiles (25th, 75th) | 620, 990 | 618, 1141
Week 6 Blood Phe Level (μmol/L)
Mean (±SD) | 607 (±377) | 891 (±348)
Percentiles (25th, 75th) | 307, 812 | 619, 1143
Mean Change in Blood Phe From Baseline to Week 6 (μmol/L)
Adjusted Mean (±SE)† | -239 (±38) | 6 (±36)
Percentiles (25th, 75th) | -397, -92 | -96, 93
Mean Percent Change in Blood Phe From Baseline to Week 6
Mean (±SD) | - 29 (±32) | 3 (±33)
Percentiles (25th, 75th) | -61, -11 | -13, 12

*The mean baseline levels shown in this table represent the mean of 3 pretreatment levels (Wk -2, Wk -1, and Wk 0). Treatment with KUVAN or placebo started at Wk 0.

†p-value < 0.001, adjusted mean and standard error from an ANCOVA model with change in blood Phe level from baseline to Week 6 as the response variable, and both treatment group and baseline blood Phe level as covariates.

Change in blood Phe was noted in the KUVAN-treated group at Week 1 and was sustained through Week 6 (Figure 2).

Study 3 was a multicenter, open-label, extension study in which 80 patients who responded to KUVAN treatment in Study 1 and completed Study 2 underwent 6 weeks of forced dose-titration with 3 different doses of KUVAN. Treatments consisted of 3 consecutive 2-week courses of KUVAN at doses of 5, then 20, and then 10 mg/kg per day. Blood Phe level was monitored after 2 weeks of treatment at each dose level. At baseline, mean (±SD) blood Phe was 844 (±398) μmol/L. At the end of treatment with 5, 10, and 20 mg/kg per day, mean (±SD) blood Phe levels were 744 (±384) μmol/L, 640 (±382) μmol/L, and 581 (±399) μmol/L, respectively (Table 7).

Table 7: Blood Phe Results From Forced Dose-Titration in Study 3

KUVAN Dose Level (mg/kg per day) | No. of Patients | Mean (±SD) Blood Phe Level (μmol/L) | Mean Changes (±SD) in Blood Phe Level From Week 0 (μmol/L)
Baseline; (No Treatment) | 80 | 844 (±398) | —
5 | 80 | 744 (±384) | ‑100 (±295)
10 | 80 | 640 (±382) | ‑204 (±303)
20 | 80 | 581 (±399) | -263 (±318)

Study 4 was a multicenter study of 90 pediatric patients with PKU, ages 4 to 12 years, who were on Phe‑restricted diets and who had blood Phe levels ≤480 μmol/L at screening. All patients were treated with open-label KUVAN 20 mg/kg per day for 8 days. Response to KUVAN was defined as a ≥30% decrease in blood Phe from baseline at Day 8. At Day 8, 50 patients (56%) had a ≥30% decrease in blood Phe.

Study 5 was an open label, single arm, multicenter trial in 93 pediatric patients with PKU, aged 1 month to 6 years, who had Phe levels greater than or equal to 360 μmol/L at screening. All patients were treated with KUVAN at 20 mg/kg per day and maintained on a Phe-restricted diet. At Week 4, 57 patients (61%) were identified as responders (defined as ≥ 30% decreased in blood Phe from baseline) [see Use in Specific Populations (8.4) Figure 1].

16 HOW SUPPLIED/STORAGE AND HANDLING

KUVAN Tablets

100 mg sapropterin dihydrochloride, are round, off-white to light yellow, mottled, and debossed with “177”. The tablets are supplied as follows:

NDC 68135-300-02 Bottle of 120 tablets

KUVAN for Oral Solution

Supplied as an off-white to yellow powder supplied in unit dose packets as follows:

100 mg sapropterin dihydrochloride per packet:

NDC 68135-301-22 Carton of 30 unit dose packets

NDC 68135-301-11 Single unit dose packet

500 mg sapropterin dihydrochloride per packet:

NDC 68135-482-11 Carton of 30 unit dose packets

NDC 68135-482-10 Single unit dose packet

Storage

Store KUVAN tablets at 20ºC to 25ºC (68ºF to 77ºF); excursions allowed between 15ºC to 30ºC (59ºF to 86ºF) [see USP Controlled Room Temperature]. Keep container tightly closed. Protect from moisture.

Store KUVAN for oral solution at 20ºC to 25ºC (68ºF to 77ºF); excursions allowed between 15ºC to 30ºC (59ºF to 86ºF) [see USP Controlled Room Temperature]. Protect from moisture.

17 PATIENT COUNSELING INFORMATION

Advise the patient or caregiver to read the FDA-approved patient labeling (Patient Information and Instructions for Use).

Hypersensitivity Reactions Including Anaphylaxis

Advise patients and caregivers to discontinue KUVAN and contact the patient’s healthcare provider immediately if they experience symptoms of anaphylaxis, including (but not limited to) wheezing, dyspnea, coughing, hypotension, flushing, nausea, and rash. Continue nutritional management including dietary protein and Phe restriction [see Warnings and Precautions (5.1)].

Upper Gastrointestinal Mucosal Inflammation

Advise patients and caregivers to contact their healthcare provider if the patient experiences signs and symptoms suggestive of upper GI mucosal inflammation, including nausea, vomiting, dysphagia, dyspepsia, loss of appetite; oropharyngeal, esophageal, or upper abdominal pain [see Warnings and Precautions (5.3)].

Hypophenylalaninemia

Advise patients and caregivers that KUVAN may cause hypophenylalaninemia (low blood Phe levels), especially in pediatric patients younger than 7 years of age [see Warnings and Precautions (5.3)].

Monitoring of Blood Phe Levels

Advise patients and caregivers that frequent blood Phe monitoring is important to ensure blood Phe levels are in the desirable range and that they should maintain dietary protein and Phe restriction while on KUVAN [see Warnings and Precautions (5.4)].

Prolonged hyperphenylalaninemia (high blood Phe levels) in patients with PKU can result in severe neurologic damage, including intellectual disability, developmental delay, microcephaly, delayed speech,seizures, and behavioral abnormalities [see Warnings and Precautions (5.4)].

Lack of Biochemical Response to KUVAN

Some patients do not show a biochemical response (blood Phe reduction) when treated with KUVAN. Advise patients and caregivers to discontinue treatment with KUVAN if the patient does not show an adequate biochemical response in blood Phe after one month of treatment with KUVAN 20 mg/kg per day [see Dosage and Administration (2.2), Warnings and Precautions (5.4)].

Interaction with Levodopa

Advise patients and caregivers that patients with underlying neurological disorders taking KUVAN in combination with levodopa may experience seizures, exacerbation of seizures, over-stimulation or irritability. Inform patients and caregivers to contact their healthcare provider if the patient has a change in neurologic status during treatment with KUVAN [see Warnings and Precautions (5.5)].

Hyperactivity

Advise patients and caregivers that KUVAN may cause hyperactivity and to contact their healthcare provider if the patient experiences hyperactivity, restlessness, fidgeting, or excessive talking [see Warnings and Precautions (5.6)].

Dosing and Monitoring [see Dosage and Administration (2.2)]

Advise patients and caregivers of the following:

- KUVAN should be used in conjunction with a PKU-specific diet, including dietary protein and Phe restriction.
- Dietary protein and Phe intake should not be modified during the KUVAN evaluation period when assessing biochemical response.
- The patient must be evaluated for changes in blood Phe after being treated with KUVAN at the recommended dose(s) for age to determine if they have a biochemical response and that blood Phe levels and dietary Phe intake should be assessed frequently during the first month of KUVAN treatment.
- Monitoring of blood Phe levels is important during KUVAN treatment.

Preparation and Administration [see Dosage and Administration (2.3)]

Advise patients and caregivers:

- KUVAN tablets can be swallowed whole, dissolved in water or apple juice, or crushed and mixed with a small amount of soft food such as apple sauce or pudding.
- KUVAN powder for oral solution should be dissolved in water or apple juice or stirred in a small amount of soft food such as apple sauce or pudding.
- Take KUVAN with a meal, preferably at the same time each day.

Manufactured for:

BioMarin Pharmaceutical Inc.

Novato, CA 94949

PATIENT INFORMATION

KUVAN (COO-van)

(sapropterin dihydrochloride)

tablets

KUVAN (COO-van)

(sapropterin dihydrochloride)

powder for oral solution

What is KUVAN?
Kuvan is a prescription medicine used to lower blood levels of phenylalanine (Phe), in adults and children one month of age and older with a certain type of Phenylketonuria (PKU). Kuvan is used along with a Phe-restricted diet.

What should I tell my doctor before taking Kuvan?

Before you take Kuvan, tell your doctor about all your medical conditions, including if you:

- are allergic to sapropterin dihydrochloride or any of the ingredients in Kuvan. See the list of ingredients in Kuvan at the end of this leaflet.
- have poor nutrition or have loss of appetite.
- are pregnant or plan to become pregnant.
  Pregnancy Exposure Registry: There is a pregnancy exposure registry for women who take Kuvan during pregnancy. The purpose of this registry is to collect information about the health of you and your baby. Talk to your doctor about how you can take part in this registry or contact the registry program at 1-800-983-4587.
- are breastfeeding or plan to breastfeed. It is not known if Kuvan passes into your breast milk. Talk to your doctor about the best way to feed your baby if you take Kuvan.

Tell your doctor about all the medicines you take, including prescription and over-the-counter medicines, vitamins, herbal, and dietary supplements. Kuvan and other medicines may interact with each other.

Especially tell your doctor if you take:

- a medicine that contains levodopa
- an antifolate medicine
- sildenafil (Revatio, Viagra), tadalafil (Adcirca, Cialis), vardenafil (Staxyn, Levitra)

Tell your doctor if you are not sure if your medicine is one that is listed above.

Know the medicines you take. Keep a list of them to show your doctor and pharmacist when you get a new medicine.

How should I take KUVAN?

- Take Kuvan exactly as your doctor tells you. Your doctor should tell you how much Kuvan to take and when to take it.
- Your doctor may change your dose of Kuvan depending on how you respond to treatment.
- Take Kuvan 1 time each day with a meal. It is best to take Kuvan at the same time each day.
- Kuvan comes as a tablet and powder for oral solution.
  - You can swallow Kuvan tablets whole or dissolve the tablets in water or apple juice. You may also crush the tablets and mix in a small amount of soft food, such as apple sauce or pudding before taking.
  - Be sure that you know what dose of Kuvan powder your doctor prescribed and whether you should use Kuvan 100 mg packets, Kuvan 500 mg packets, or both types of packets to prepare your dose.
  - Open Kuvan powder packets only when you are ready to use them.
  - Kuvan powder for oral solution should be dissolved in water or apple juice. You may also mix the powder for oral solution in a small amount of soft food, such as apple sauce or pudding before taking.
  - See the detailed “Instructions for Use” that comes with Kuvan for information about the correct way to dissolve and take a dose of Kuvan tablets or Kuvan powder for oral solution.

- It is not possible to know if Kuvan will work for you until you start taking Kuvan. Your doctor will check your blood Phe levels when you start taking Kuvan to see if the medicine is working.

- During treatment with Kuvan:
  - Any change you make to your diet may affect your blood Phe level. Follow your doctor’s instructions carefully and do not make any changes to your dietary Phe intake without first talking with your doctor. Even if you take Kuvan, if your Phe blood levels are not well controlled, you can develop severe neurologic problems.
  - Your doctor should continue to monitor your blood Phe levels often during your treatment with Kuvan, to make sure that your blood Phe levels are not too high or too low.
  - If you have a fever, or if you are sick, your blood Phe level may go up. Tell your doctor as soon as possible so they can change your dose of Kuvan to help keep your blood Phe levels in the desired range.

- If you forget to take your dose of Kuvan, take it as soon as you remember that day. Do not take 2 doses in a day.
- If you take too much Kuvan, call your doctor for advice.

What are the possible side effects of KUVAN?

Kuvan can cause serious side effects, including:

- Severe allergic reactions. Stop taking Kuvan and get medical help right away if you develop any of these symptoms of a severe allergic reaction:

- wheezing or trouble breathing
- coughing
- feeling lightheaded or you faint

- flushing
- nausea
- rash

- Inflammation of the lining of the stomach (gastritis) or esophagus (esophagitis). Gastritis or esophagitis can happen with Kuvan and may be severe. Call your doctor right away if you have any of these signs or symptoms:
  - severe upper stomach-area (abdominal) discomfort or pain, nausea and vomiting
  - blood in your vomit or stool
  - black, tarry stools
  - difficulty swallowing
  - loss of appetite
  - pain in the throat
- Phe levels that are too low. Some children under the age of 7 years who take high doses of Kuvan each day may experience low Phe levels.
- Too much or constant activity (hyperactivity) can happen with Kuvan. Tell your doctor if you have any signs of hyperactivity, including:
  - fidgeting or moving around too much
  - talking too much

The most common side effects of Kuvan are:

- headache
- runny nose and nasal congestion
- sore throat
- diarrhea
- vomiting
- cough

Tell your doctor if you have any side effect that bothers you or that does not go away.

These are not all the possible side effects of Kuvan. For more information, ask your doctor or pharmacist. Call your doctor for medical advice about side effects. You may report side effects to FDA at 1-800-FDA-1088.

How should I store KUVAN?

- Store Kuvan at room temperature between 68°F to 77°F (20°C to 25°C).
- Keep Kuvan tablets in the original bottle with the cap closed tightly.
- Protect from moisture.

Keep Kuvan and all medicines out of the reach of children.

General information about the safe and effective use of KUVAN.
Medicines are sometimes prescribed for purposes other than those listed in a Patient Information leaflet. Do not use Kuvan for a condition for which it was not prescribed. Do not give Kuvan to other people, even if they have the same symptoms you have. It may harm them. You can ask your pharmacist or doctor for information about Kuvan that is written for health professionals.

What are the ingredients in KUVAN?

Active ingredient: sapropterin dihydrochloride.

Kuvan tablet inactive ingredients: ascorbic acid, crospovidone, dibasic calcium phosphate, D‑mannitol, riboflavin, and sodium stearyl fumarate.

Kuvan powder for oral solution inactive ingredients: ascorbic acid, D‑mannitol, potassium citrate, and sucralose.

Manufactured by:

BioMarin Pharmaceutical Inc.

Novato, CA 94949

© BioMarin Pharmaceutical Inc. All rights reserved.

Kuvan is a registered trademark of BioMarin Pharmaceutical Inc.

For more information, go to www.kuvan.com or call 1-877-695-8826.

This Patient Information has been approved by the U.S. Food and Drug Administration

Revised: 03/2020

INSTRUCTIONS FOR USE

Kuvan (COO-van)

(sapropterin dihydrochloride)

tablets

Kuvan (COO-van)

(sapropterin dihydrochloride)

powder for oral solution

Read this Instructions for Use before you start taking Kuvan and each time you refill your prescription. There may be new information. This information does not take the place of talking with your healthcare provider about your treatment. Talk to your doctor if you have any questions about the right dose of Kuvan to take or how to mix it.

Important information:

- Kuvan comes as a tablet or in a packet containing powder.
- Take Kuvan exactly as your doctor tells you. Your doctor should tell you how much Kuvan to take and when to take it.
- Your doctor may change your dose of Kuvan depending on how you respond to treatment, or based on your baby’s weight.
- If your baby weighs 22 pounds or less, follow the section called “Instructions for giving Kuvan powder for oral solution (Kuvan 100 mg packets) to babies who weigh 22 pounds or less”.
- Take Kuvan 1 time each day with a meal. It is best to take Kuvan at the same time each day.

Instructions for taking Kuvan tablets:

Kuvan tablets can be swallowed whole or dissolved in water or apple juice. You may also crush the tablets and mix in a small amount of soft food, such as apple sauce or pudding.

To dissolve Kuvan tablets:

- Mix Kuvan tablets in 4 ounces to 8 ounces (½ cup to 1 cup) of water or apple juice. It may take a few minutes for the tablets to dissolve. To make the tablets dissolve faster, you can stir or crush them.
- The tablets may not dissolve completely. You may see small pieces floating on top of the water or apple juice. This is normal and safe for you to swallow.
- Drink within 15 minutes.
- After drinking your medicine, if you still see small pieces of the tablet, add more water or apple juice and drink to make sure that you take all of your medicine.

Instructions for taking Kuvan powder for oral solution:

For babies who weigh 22 pounds or less, see the section below called “Instructions for giving Kuvan powder for oral solution (Kuvan 100 mg packets) to babies who weigh 22 pounds or less.”

Kuvan powder for oral solution should be dissolved in water or apple juice. The powder for oral solution may also be mixed in a small amount of soft foods, such as apple sauce or pudding.

To dissolve Kuvan powder for oral solution:

- Be sure that you know what dose of Kuvan your doctor has prescribed and whether you should use Kuvan 100 mg packets, Kuvan 500 mg packets, or both types of packets to prepare your dose.
- Open the packet(s) of Kuvan powder for oral solution by folding and tearing, or cutting at the dotted line in the upper right corner of the packet. Open the packet(s) only when you are ready to use them.
- Empty the contents of the packet(s) into 4 ounces to 8 ounces (1/2 cup to 1 cup) of water or apple juice.
- Drink within 30 minutes.

Instructions for giving Kuvan powder for oral solution (Kuvan 100 mg packets) to babies who weigh 22 pounds or less:

- The dose of Kuvan is based on body weight. This will change as your baby grows. Your doctor will tell you:
  - the number of Kuvan 100 mg packets needed for one dose
  - the amount of water or apple juice needed to mix one dose of Kuvan
  - the amount of the mixture (powder and water or apple juice) you will need to give your baby his or her prescribed dose of medicine.
- Give your baby the prescribed amount of mixture (powder and water or apple juice) within 30 minutes after mixing. If you are not able to give your baby’s dose within 30 minutes after mixing, pour the unused medicine into the trash. You will need to mix a new dose.

Supplies needed to mix and give your baby’s dose of Kuvan powder for oral solution:

- the number of Kuvan 100 mg packets needed for one dose
- a small cup of water or apple juice
- one 30 mL medicine cup for mixing
- small spoon or clean utensil for mixing
- 10 mL oral dosing syringe
- scissors (optional)

Ask your pharmacist for a 30 mL medicine cup for mixing and an oral dosing syringe if you do not have these supplies.

Step 1: | Find a clean, flat work surface.
Step 2: | Place a small cup of water or apple juice, the oral dosing syringe, and an empty medicine cup on your clean, flat work surface (see Figure A). | Figure A
Step 3: | Pour 5 mL or 10 mL of water or apple juice from the small cup into the medicine cup, as instructed by your doctor. Check to make sure that the amount of liquid lines up with the amount that your doctor tells you (see Figure B). | Figure B
Step 4: | Check the label on the Kuvan packet(s). If the packet is marked Kuvan 100 mg, empty the entire contents of the Kuvan packet into the medicine cup (see Figure C). | Figure C
Step 5: | Stir the mixture with the small spoon or other clean utensil until all of the powder completely dissolves (see Figure D). | Figure D
Step 6: | To give a dose of Kuvan to your baby: Place the tip of the oral dosing syringe into the liquid inside the medicine cup. Pull back on the plunger and draw up the amount of the mixture prescribed by your doctor (see Figure E). | Figure E
Step 7: | Take the oral dosing syringe out of the medicine cup. Carefully turn the oral dosing syringe so that the tip is pointing up. Check to make sure that the amount of medicine in the oral dosing syringe lines up with the amount of mixture prescribed by your doctor (see Figure F). | Figure F
Step 8: | Place the tip of the oral dosing syringe into your baby’s mouth. Point the tip of the oral dosing syringe toward either cheek (see Figure G). Push on the plunger slowly, a small amount at a time, until all of the mixture in the oral dosing syringe is given. | Figure G
Step 9: | Throw away any remaining mixture. Remove the plunger from the barrel of the oral dosing syringe. Wash the oral dosing syringe and medicine cup with warm water and air dry. When the oral dosing syringe is dry, put the plunger back into the barrel. Store the oral dosing syringe and medicine cup for the next use.

How should I store Kuvan?

- Store Kuvan at room temperature between 68°F to 77°F (20°C to 25°C).
- Keep Kuvan tablets in the original bottle with the cap closed tightly.
- Protect from moisture.

Keep Kuvan and all medicines out of the reach of children.

This Instructions for Use has been approved by the U.S. Food and Drug Administration.

BioMarin Pharmaceutical Inc.

Novato, CA 94949

Revised: 07/2015

© BioMarin Pharmaceutical Inc. All rights reserved.

Kuvan is a registered trademark of BioMarin Pharmaceutical Inc.

v2/2015

100 MG TABLETS

NDC 68135-300-02
KUVAN®

(sapropterin dihydrochloride) Tablets
100 mg*
* Equivalent to 76.8 mg of sapropterin
Rx only
120 Tablets
BIOMARIN®

100 MG POWDER FOR ORAL SOLUTION

NDC 68135-301-22

KUVAN®

(sapropterin dihydrochloride)

Powder for Oral Solution

100 mg*

Rx only

30 individual packets per carton

BIOMARIN®

500 MG POWDER FOR ORAL SOLUTION

NDC 68135-482-11

KUVAN®

(sapropterin dihydrochloride)

Powder for Oral Solution

500 mg* per single use packet

* Equivalent to 384 mg of sapropterin

Rx only

30 individual packets per carton

BIOMARIN®